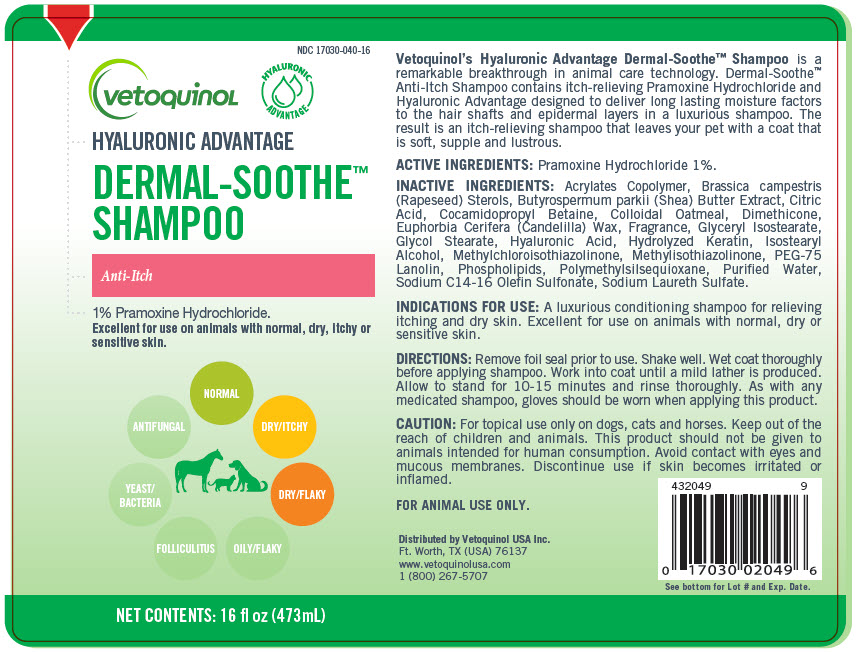 DRUG LABEL: Dermal-Soothe
NDC: 17030-040 | Form: SHAMPOO
Manufacturer: Vetoquinol USA, Inc.
Category: animal | Type: OTC ANIMAL DRUG LABEL
Date: 20260106

ACTIVE INGREDIENTS: Pramoxine Hydrochloride 10 mg/1 mL
INACTIVE INGREDIENTS: Water; Cocamidopropyl Hydroxysultaine; Cocamidopropyl Betaine; Ammonium Laureth-2 Sulfate; Cetyl Alcohol; PEG-75 Lanolin; Oatmeal; Glycol Stearate; Citric Acid Monohydrate; METHYLCHLOROISOTHIAZOLINONE

Dermal-Soothe™

Patented Continuous
Moisture Release

INDICATIONS:

A luxurious conditioning shampoo for relieving itching and dry skin. Excellent for use on animals with normal, dry or sensitive skin.

DESCRIPTION:

Micro Pearls® Advantage Dermal-Soothe™ Anti-Itch Shampoo is a remarkable breakthrough in animal care technology. Dermal-Soothe™ Anti-Itch Shampoo contains itch-relieving Pramoxine Hydrochloride and Novasome® microvesicles designed to deliver long lasting moisture factors to the hair shafts and epidermal layers in a luxurious shampoo. The result is an itch-relieving shampoo that leaves your pet with a coat that is soft, supple and lustrous.

DIRECTIONS:

Remove foil seal prior to use. Shake well. Wet coat thoroughly before applying shampoo. Work into coat until a mild lather is produced. Allow to stand for 10-15 minutes and rinse thoroughly. As with any medicated topical product, gloves should be worn when applying this product.

ACTIVE INGREDIENTS:

Pramoxine Hydrochloride 1%

INACTIVE INGREDIENTS:

USP Purified Water, Decyl Polyglucose, Cocamidopropyl Hydroxysultaine, NM7, Cocamidopropyl Betaine, Ammonium Laureth Sulfate, Cetyl Alcohol, PEG 75 Lanolin, Hydrolyzed Keratin, Colloidal Oatmeal, Glycol Stearate, Citric Acid, Fragrance, Methylchloroisothiazolinone, Methylisothiazolinone and Skin Respiratory Factor.

CAUTIONS:

For topical use only on dogs, cats and horses. Avoid contact with eyes and mucous membranes. Discontinue use if skin becomes irritated or inflamed.

KEEP OUT OF REACH OF CHILDREN.
FOR ANIMAL USE ONLY.

Novasome® is a registered trademark of Micro Pak, Inc.

QUESTIONS?

Manufactured for:
Vetoquinol USA, Inc.
Ft. Worth, TX (USA) 76137
1 (800) 267-5707
www.vetoquinolusa.com

422629
5

Lot

Exp. Date

PRINCIPAL DISPLAY PANEL - 473 mL Bottle Label

NDC 17030-040-16

vetoquinoL

HYALURONIC
ADVANTAGE

HYALURONIC ADVANTAGE

DERMAL-SOOTHE™
SHAMPOO

Anti-Itch

1% Pramoxine Hydrochloride.
Excellent for use on animals with normal, dry, itchy or
sensitive skin.

YEAST/
BACTERIA
ANTIFUNGAL
NORMAL
DRY/ITCHY
DRY/FLAKY
OILY/FLAKY
FOLLICULITUS

NET CONTENTS: 16 fl oz (473mL)